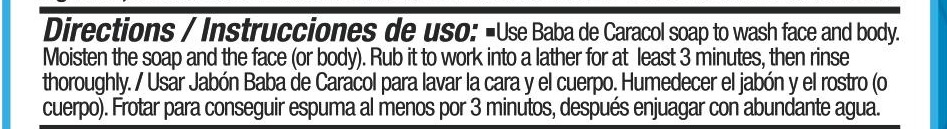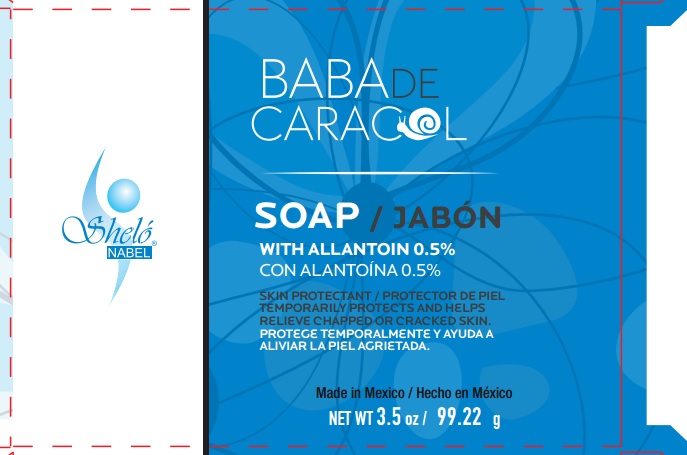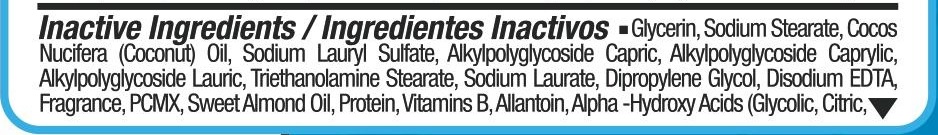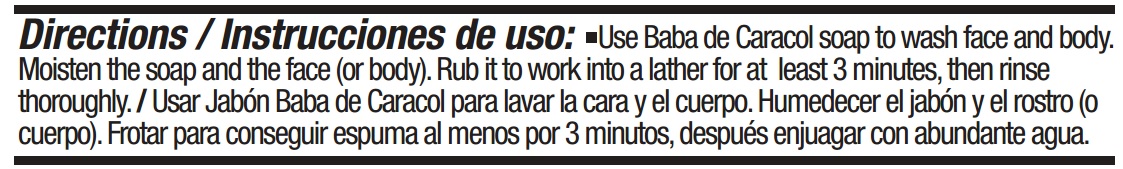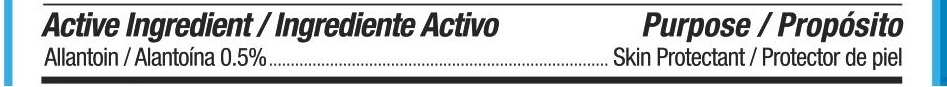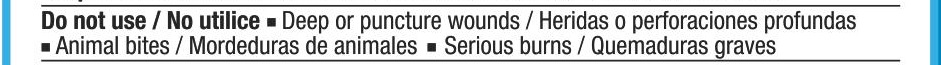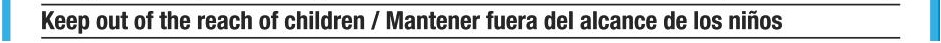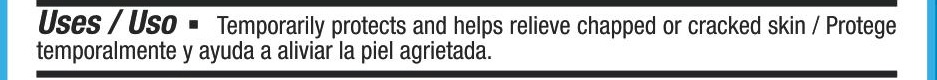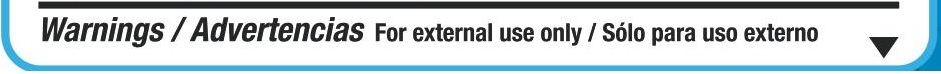 DRUG LABEL: Jabon Shelo Nabel Con Alantoina Baba de Caracol
NDC: 71424-7713 | Form: SOAP
Manufacturer: Corporativo Serysi S de R L de C V
Category: otc | Type: HUMAN OTC DRUG LABEL
Date: 20191015

ACTIVE INGREDIENTS: ALLANTOIN 5 mg/1 g
INACTIVE INGREDIENTS: GLYCERIN

Soap Shelo NABEL BC 3.5 Oz. / Jabon Shelo NABEL 99 Grs.